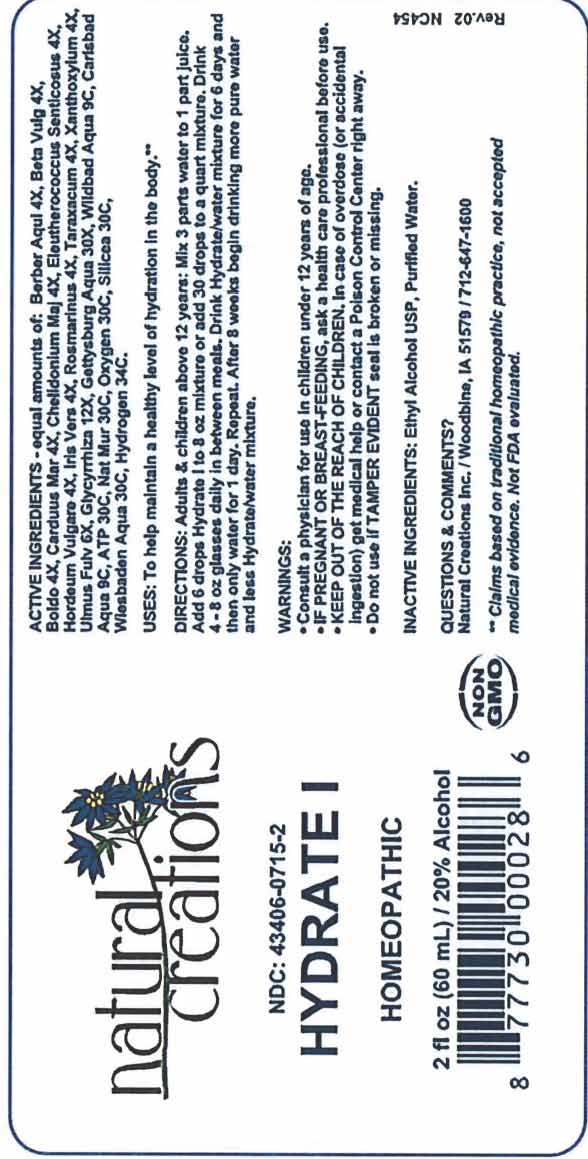 DRUG LABEL: Hydrate 1
NDC: 43406-0715 | Form: LIQUID
Manufacturer: Natural Creations, Inc
Category: homeopathic | Type: HUMAN OTC DRUG LABEL
Date: 20251216

ACTIVE INGREDIENTS: BERBERIS AQUIFOLIUM ROOT BARK 4 [hp_X]/1 mL; BETA VULGARIS WHOLE 4 [hp_X]/1 mL; PEUMUS BOLDUS LEAF 4 [hp_X]/1 mL; MILK THISTLE 4 [hp_X]/1 mL; CHELIDONIUM MAJUS WHOLE 4 [hp_X]/1 mL; ELEUTHEROCOCCUS SENTICOSUS WHOLE 4 [hp_X]/1 mL; HORDEUM VULGARE WHOLE 4 [hp_X]/1 mL; IRIS VERSICOLOR ROOT 4 [hp_X]/1 mL; SALVIA ROSMARINUS FLOWERING TOP 4 [hp_X]/1 mL; TARAXACUM OFFICINALE 4 [hp_X]/1 mL; ULMUS RUBRA BARK 6 [hp_X]/1 mL; ZANTHOXYLUM AMERICANUM BARK 4 [hp_X]/1 mL; GLYCYRRHIZA GLABRA 12 [hp_X]/1 mL; ADENOSINE TRIPHOSPHATE 30 [hp_C]/1 mL; HYDROGEN 34 [hp_C]/1 mL; SODIUM CHLORIDE 30 [hp_C]/1 mL; OXYGEN 30 [hp_C]/1 mL; SILICON DIOXIDE 30 [hp_C]/1 mL
INACTIVE INGREDIENTS: ALCOHOL; WATER

HYDRATE 1

ACTIVE INGREDIENT

ACTIVE INGREDIENTS: equal amounts of: Berber Aqui 4X, Beta Vulg 4X, Boldo 4X, Carduus Mar 4X, Chelidonium Maj 4X, Eleutherococcus Senticosus 4X, Hordeum Vulgare 4X, Iris Vers 4X, Rosmarinus 4X, Taraxacum 4X, Xanthoxylum 4X, Ulmus Fulv 6X, Glycyrrhiza 12X, Gettysburg Aqua 30X, Wildbad Aqua 9C, Carlsbad Aqua 9C, ATP 30C, Nat Mur 30C, Oxygen 30C, Silicea 30C, Wiesbaden Aqua 30C, Hydrogen 34C.

INDICATIONS AND USAGE

USES: To help maintain a healthy level of hydration in the body.**

PURPOSE

USES: To help maintain a healthy level of hydration in the body.**

DOSAGE AND ADMINISTRATION

DIRECTIONS: Adults & children above 12 years: Mix 3 parts water to 1 part juice. Add 6 drops Hydrate I to 8oz mixture or add 30 drops to a quart mixture. Drink 4 - 8 oz glasses daily between meals. Drink Hydrate/water mixture for 6 days and then only water for 1 day. Repeat. After 8 weeks begin drinking more pure water and less Hydrate/water mixture.

KEEP OUT OF REACH OF CHILDREN

KEEP OUT OF THE REACH OF CHILDREN. In case of overdose (or accidental ingestion) get medical help or contact a Poison Control Center right away.

WARNINGS:

- Consult a physician for use in children under 12 years of age.
- IF PREGNANT OR BREAST-FEEDING, ask a health care professional before use.
- KEEP OUT OF THE REACH OF CHILDREN. In case of overdose (or accidental ingestion) get medical help or contact a Poison Control Center right away.
- Do not use if TAMPER EVIDENT seal is broken or missing.

INACTIVE INGREDIENTS: Ethyl Alcohol USP, Purified Water.

QUESTIONS & COMMENTS?

Natural Creations, Inc. / Woodbine, IA 51579 / 712-647-1600

REFERENCES

**Claims based on traditional homeopathic practice, not accepted medical evidence. Not FDA evaluated.

PACKAGE LABEL

NDC: 43406-0715-2

HYDRATE I

HOMEOPATHIC

2 fl oz (60 mL) / 20% Alcohol